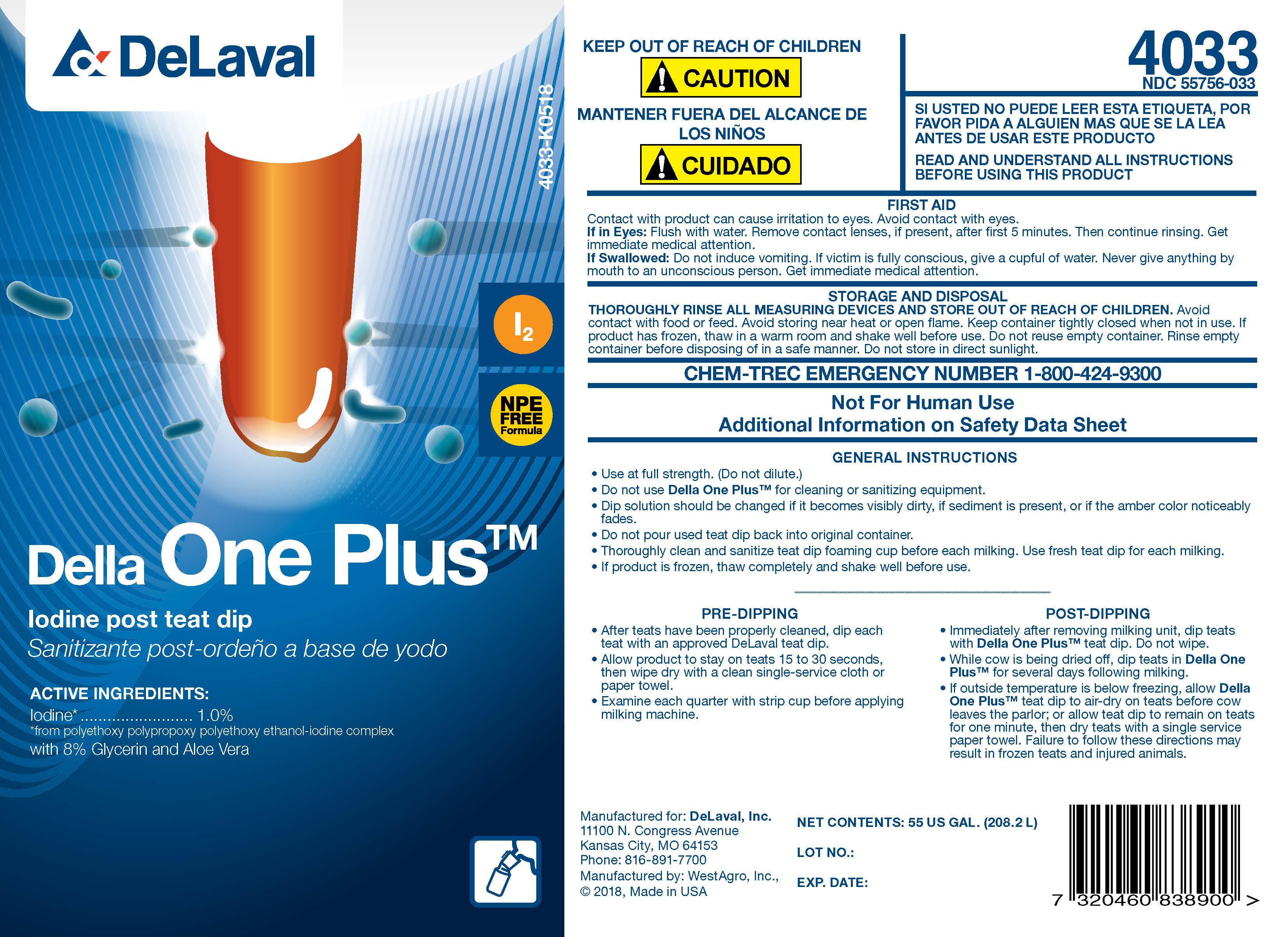 DRUG LABEL: Della One Plus
NDC: 55756-033 | Form: SOLUTION
Manufacturer: DeLaval
Category: animal | Type: OTC ANIMAL DRUG LABEL
Date: 20230216

ACTIVE INGREDIENTS: IODINE 10.5 g/1 L

DeLaval Della One Plus

ACTIVE INGREDIENT

Iodine post test dip
Sanitizante post-ordeno a base de yodo

ACTIVE INGREDIENTS:

Iodine ................................. 1%
from polyethoxy polypropoxy polyethoxy ethanol-iodine complex
with 8% Glycerin and Aloe Vera

4033-I0116

I2

NPE FREE Formula

KEEP OUT OF REACH OF CHILDREN
! CAUTION

MANTENER FUERA DEL ALCANCE DE LOST NINOX
! CUIDADO

SI USTED NO PUEDE LEER ESTA ETIQUETA POR FAVOR PIDA A ALGUIEN MAS QUESE LA LEA ANTES DE USAR ESTE PRODUCTO

READ AND UNDERSTAND ALL INSTRUCTIONS BEFORE USING THIS PRODUCT

FIRST AID
Contact with product can cause irritation to eyes. Avoid contact with eyes.
Eye Contact: Flush with water. Remove contact lenses, if present, after first 5 minutes. Then continue rinsing. Get immediate medical attention.
If Swallowed: Do not induce vomiting. If victim is fully conscious, give a cupful of water. Never give anything by mouth to an unconscious person. Get immediate medical attention.

STORAGE AND DISPOSAL

THOROUGHLY RINSE ALL MEASURING DEVICES AND STORE OUT OF REACH OF CHILDREN. Avoid contact with food or feed. Avoid storing near heat or open flame. Keep container tightly closed when not in use. If product has frozen, thaw in a warm room and shake well before use. Do not reuse empty container. Rinse empty container before disposing of in a safe manner. Do not store in direct sunlight.

CHEM-TREC EMERGENCY NUMBER 1-800-424-9300

Not For Human Use

Additional Information on Material Safety Data Sheet

INDICATIONS AND USAGE

GENERAL INSTRUCTIONS

- Use at full strength. (Do not dilute.)
- Do not use Della One Plus for cleaning or sanitizing equipment.
- Dip solution should be changed if it becomes visibly dirty, if sediment is present, or if the amber color noticeably fades.
- Do not pour used teat dip back into the original container.
- Thoroughly clean and sanitize teat dip foaming cup before each milking. Use fresh teat dip for each milking.
- If product is frozen, thaw completely and shake well before use.

PRE-DIPPING

- After teats have been properly cleaned, dip each teat with an approved DeLaval teat dip.
- Allow product to stay on tests 15 to 30 seconds, then wipe dry with a clean single-service cloth or paper towel.
- Examine each quarter with strip cup before applying milking machine.

POST-DIPPING

- Immediately after removing milking unit, dip teats with Della One Plus teat dip. Do not wipe.
- While cow is being dried off, dip teats in Della One Plus for several days following milking.
- If outside temperature is below freezing, allow DeLaval Prima Teat dip to air-dry on teats before cow leaves the parlor; or allow teat dip to remain on teats for one minute, then dry teats with a single service paper towel. Failure to follow these directions may result in frozen teats and injured animals.

Manufactured for: DeLaval, Inc.
11100 N. Congress Avenue
Kansas City, MO 64153
Phone: 816-891-7700
Manufactured by: WestAgro, Inc.
©2018, Made in USA

NET CONTENTS:

LOT NO.:

EXP. DATE: